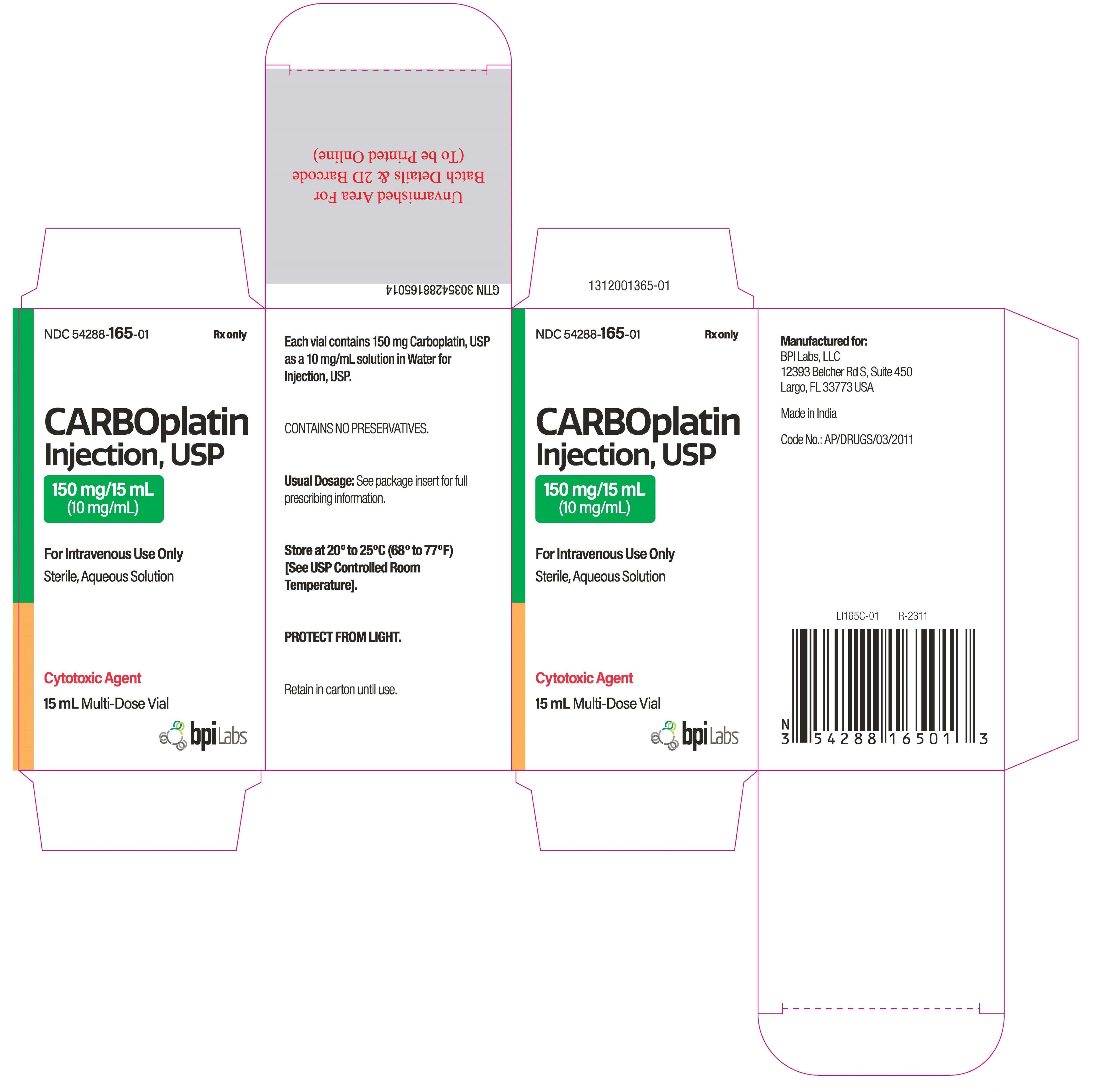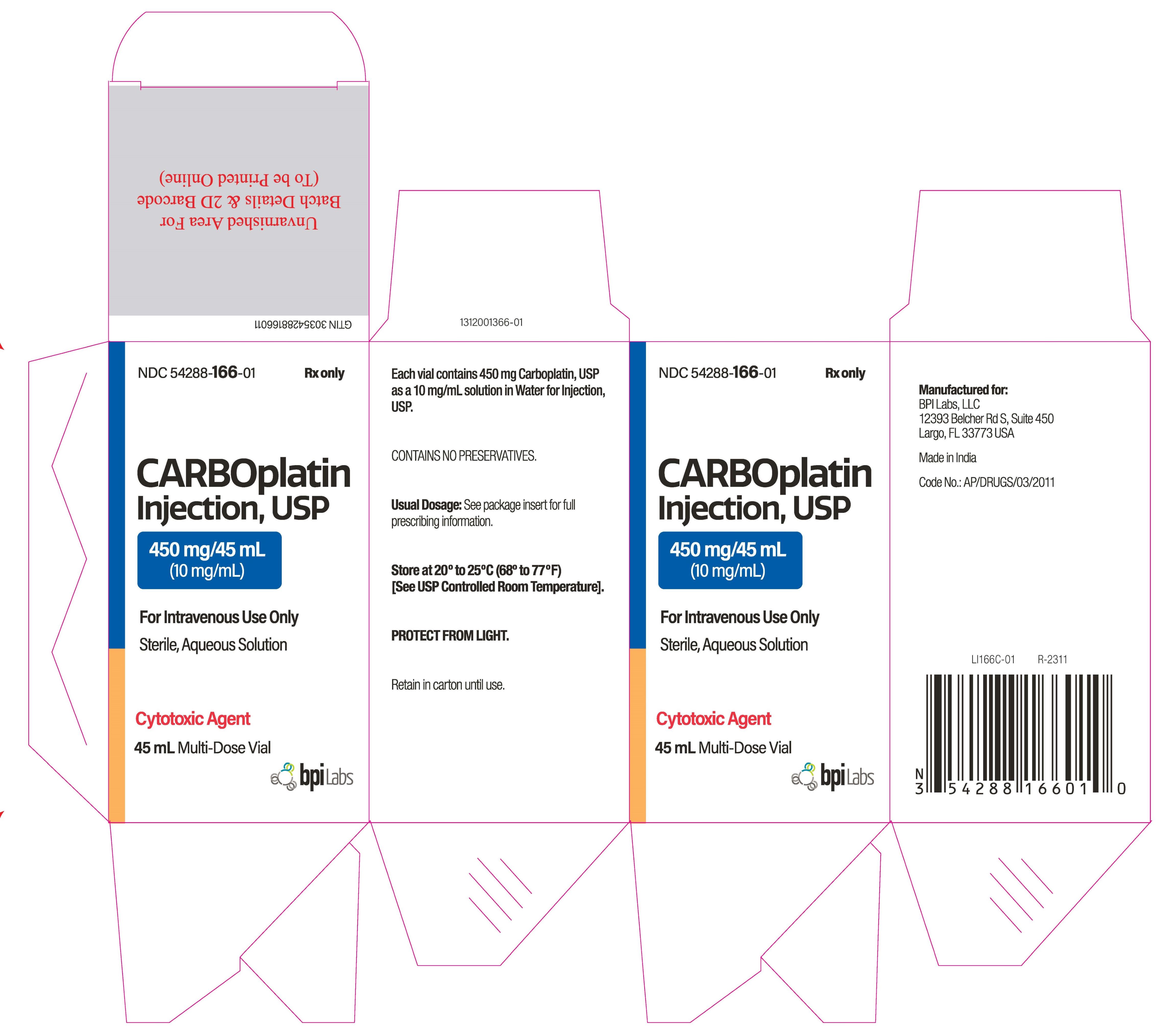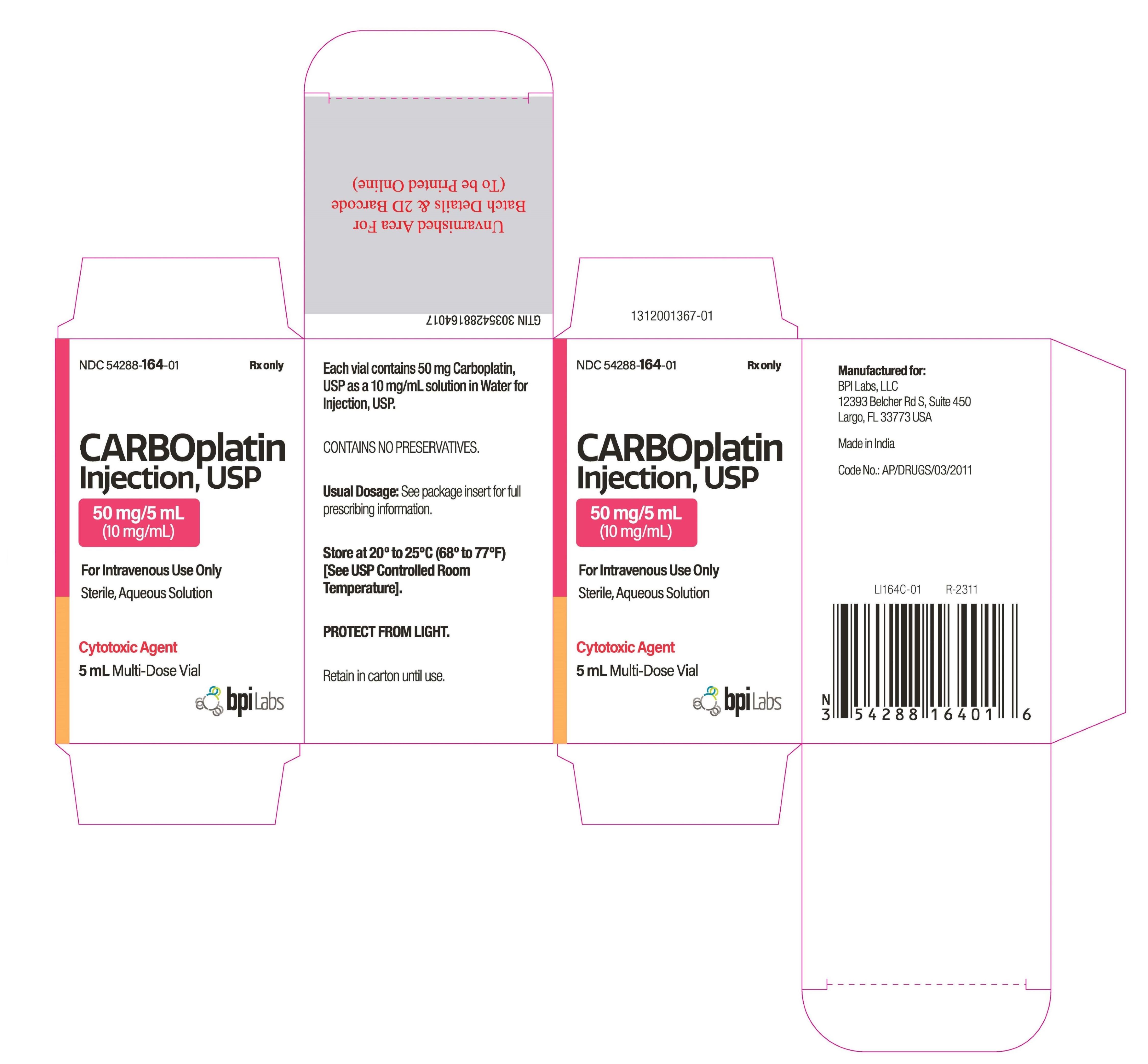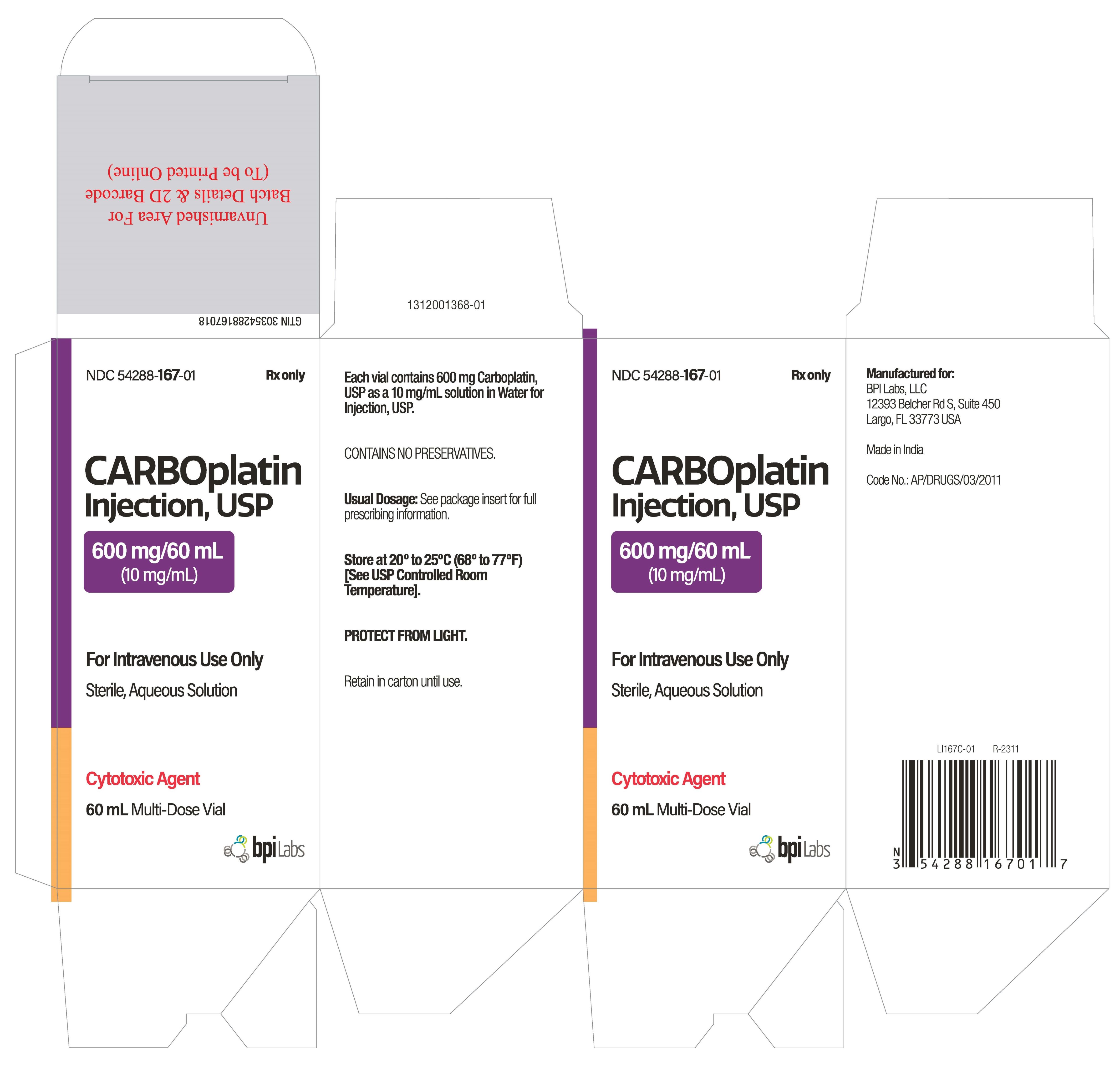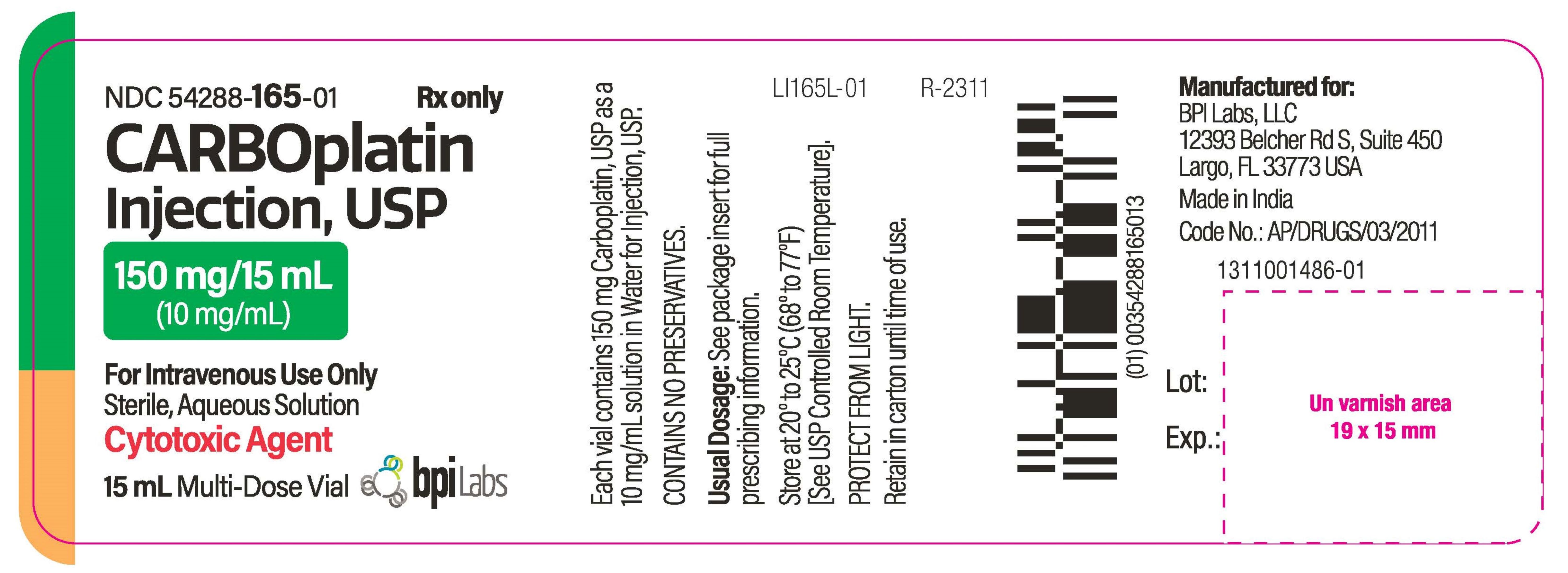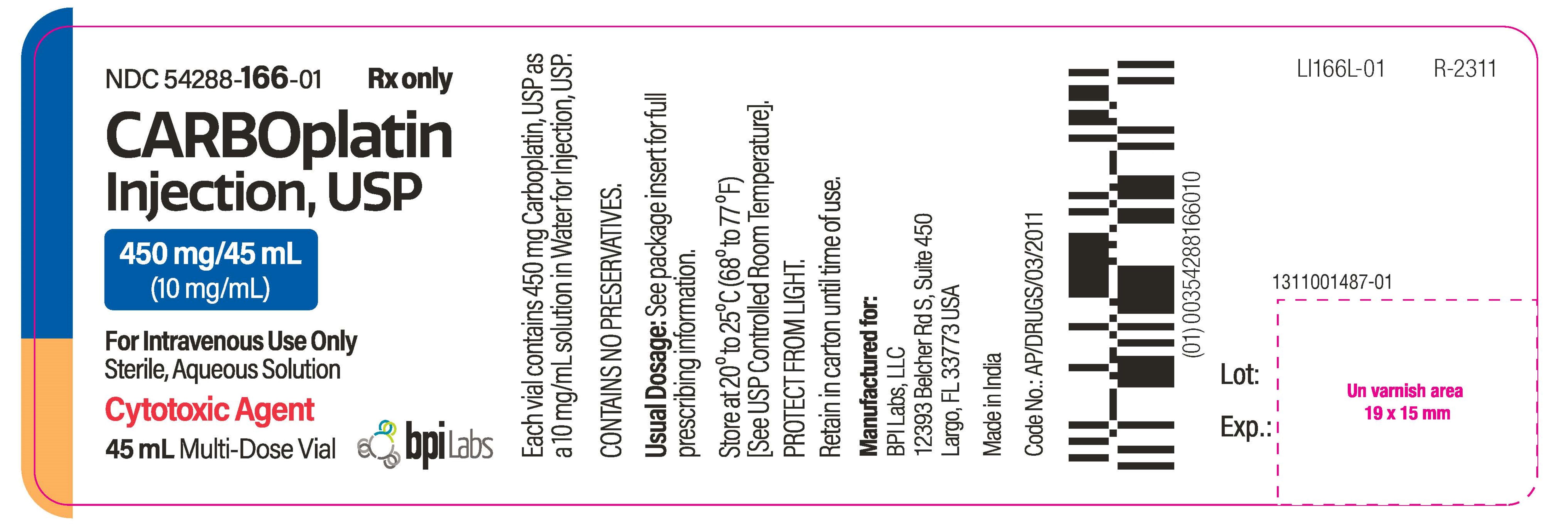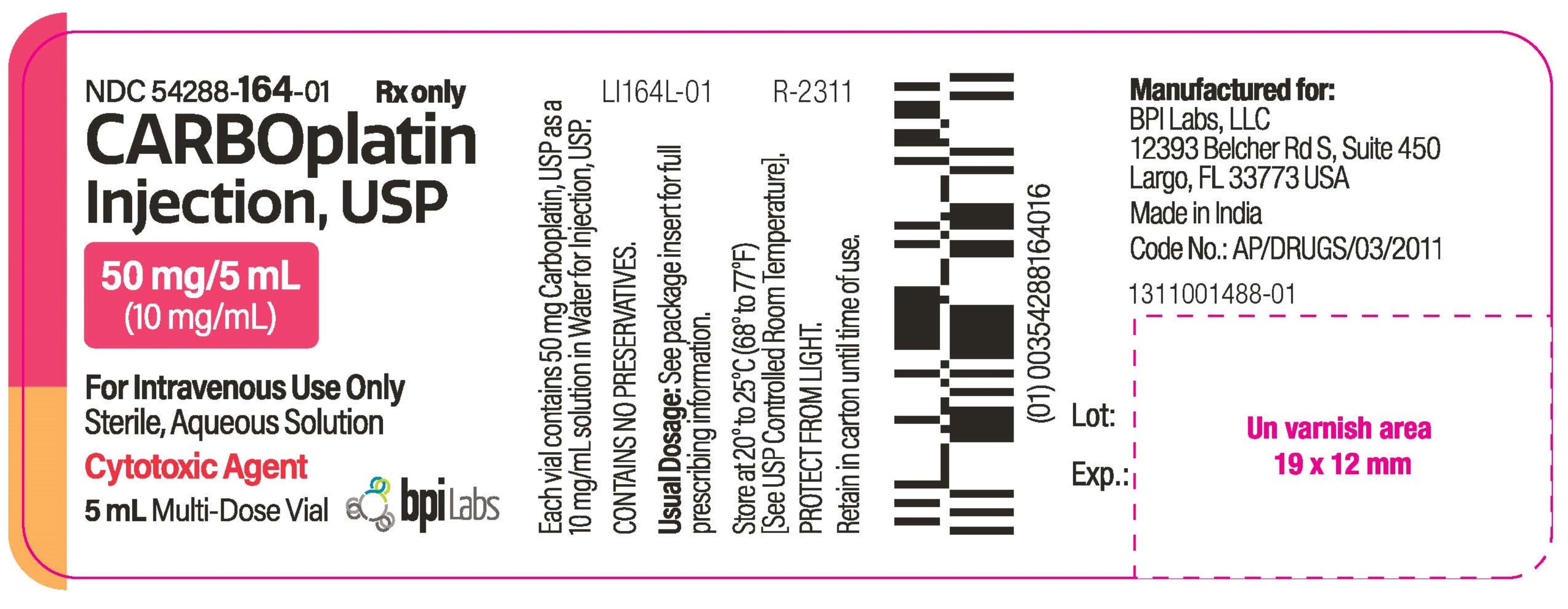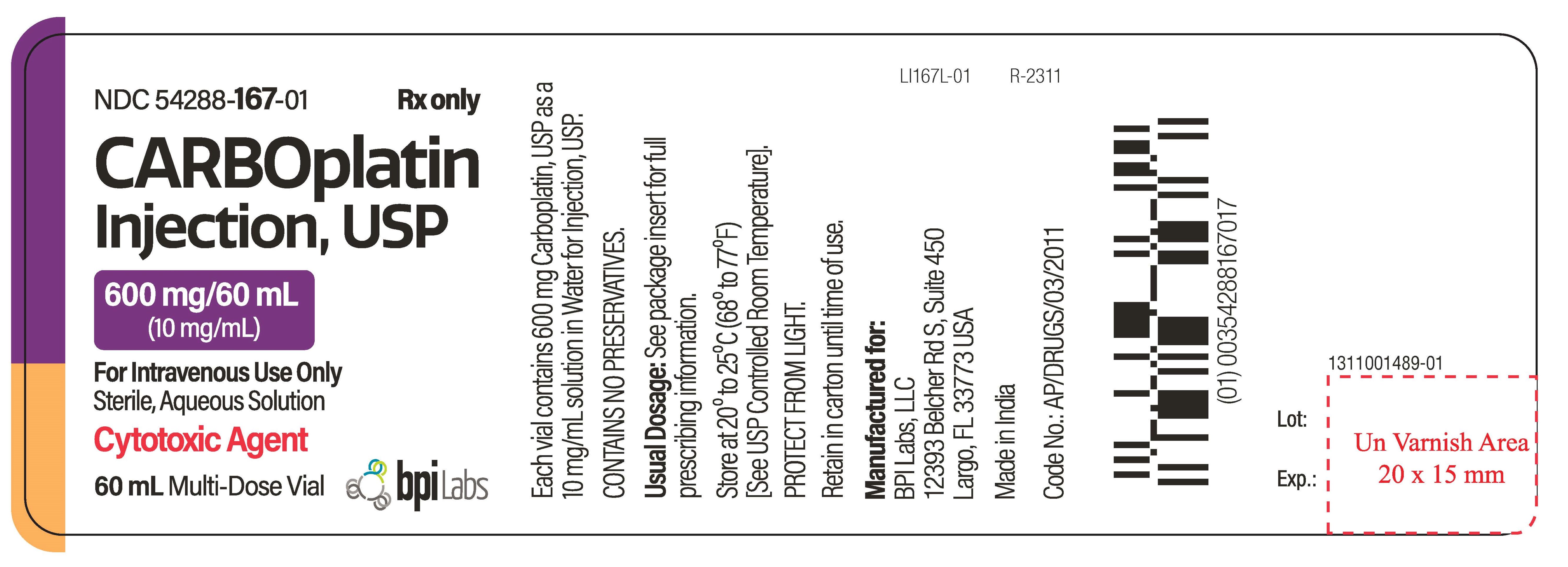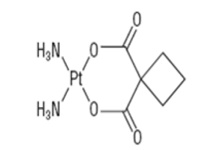 DRUG LABEL: CARBOPLATIN
NDC: 54288-165 | Form: INJECTION, SOLUTION
Manufacturer: BPI Labs LLC
Category: prescription | Type: HUMAN PRESCRIPTION DRUG LABEL
Date: 20251226

ACTIVE INGREDIENTS: CARBOPLATIN 10 mg/1 mL
INACTIVE INGREDIENTS: WATER

CARBOPLATIN- carboplatin injection, USP solution
Rx only

BOXED WARNING

Carboplatin injection should be administered under the supervision of a qualified physician experienced in the use of cancer chemotherapeutic agents. Appropriate management of therapy and complications is possible only when adequate treatment facilities are readily available.

Bone marrow suppression is dose related and may be severe, resulting in infection and/or bleeding. Anemia may be cumulative and may require transfusion support. Vomiting is another frequent drug related side effect.
Anaphylactic-like reactions to carboplatin have been reported and may occur within minutes of carboplatin injection administration. Epinephrine, corticosteroids, and antihistamines have been employed to alleviate symptoms.

DESCRIPTION

Carboplatin injection,USP is supplied as a sterile, pyrogen-free, 10 mg/mL aqueous solution of carboplatin, USP. Carboplatin, USP is a platinum coordination compound. The chemical name for carboplatin, USP is platinum, diammine [1,1-cyclobutane dicarboxylato(2-)-0,0’]-,(SP-4-2), and carboplatin, USP has the following structural formula:

C6H12N2O4Pt M.W. 371.25
Carboplatin, USP is a crystalline powder. It is soluble in water at a rate of approximately 14 mg/mL, and the pH of a 1% solution is 5 to 7. It is virtually insoluble in ethanol, acetone, and dimethylacetamide.

CLINICAL PHARMACOLOGY

Carboplatin, like cisplatin, produces predominantly inter strand DNA cross-links rather than DNA-protein cross-links. This effect is apparently cell-cycle nonspecific. The aquation of carboplatin, whichis thought to produce the active species, occurs at a slower rate than in the case of cisplatin. Despite this difference, it appears that both carboplatin and cisplatin induce equal numbers of drug-DNA cross-links, causing equivalent lesions and biological effects. The differences in potencies for carboplatin and cisplatin appear to be directly related to the difference in aquation rates.
In patients with creatinine clearances of about 60 mL/min or greater, plasma levels of intact carboplatin decay in a biphasic manner after a 30-minute intravenous infusion of 300 mg/m^2 to 500 mg/m^2 of carboplatin. The initial plasma half-life (alpha) was found to be 1.1 to 2 hours (n = 6), and the postdistribution plasma half-life (beta) was found to be 2.6 to 5.9 hours (n = 6). The total body clearance, apparent volume of distribution and mean residence time for carboplatin are 4.4 L/hour, 16 L and 3.5 hours, respectively. The C maxvalues and areas under the plasma concentration versus time curves from 0 to infinity (AUC inf) increase linearly with dose, although the increase was slightly more than dose proportional. Carboplatin, therefore, exhibits linear pharmacokinetics over the dosing range studied (300 mg/m^2 to 500 mg/m^2).
Carboplatin is not bound to plasma proteins. No significant quantities of protein-free, ultrafilterable platinum-containing species other than carboplatin are present in plasma. However, platinum from carboplatin becomes irreversibly bound to plasma proteins and is slowly eliminated with a minimum half-life of 5 days.
The major route of elimination of carboplatin is renal excretion. Patients with creatinine clearances of approximately 60 mL/min or greater excrete 65% of the dose in the urine within 12 hours and 71% of the dose within 24 hours. All of the platinum in the 24-hour urine is present as carboplatin. Only 3% to 5% of the administered platinum is excreted in the urine between 24 and 96 hours. There are insufficient data to determine whether biliary excretion occurs.
In patients with creatinine clearances below 60 mL/min, the total body and renal clearances of carboplatin decrease as the creatinine clearance decreases. Carboplatin dosages should therefore be reduced in these patients (see DOSAGE AND ADMINISTRATION).
The primary determinant of carboplatin injection clearance is glomerular filtration rate (GFR) and this parameter of renal function is often decreased in elderly patients. Dosing formulas incorporating estimates of GFR (see DOSAGE AND ADMINISTRATION) to provide predictable carboplatin injection plasma AUCs should be used in elderly patients to minimize the risk of toxicity.
CLINICAL STUDIES
Use with Cyclophosphamide for Initial Treatment of Ovarian Cancer
In two prospectively randomized, controlled studies conducted by the National Cancer Institute of Canada, Clinical Trials Group (NCIC) and the Southwest Oncology Group (SWOG), 789 chemotherapy naive patients with advanced ovarian cancer were treated with carboplatin or cisplatin, both in combination with cyclophosphamide every 28 days for 6 courses before surgical reevaluation. The following results were obtained from both studies:
Comparative Efficacy
Overview of Pivotal Trials

 | NCIC | SWOG
Number of patients randomized | 447 | 342
Median age (years) | 60 | 62
Dose of cisplatin | 75 mg/m^2 | 100 mg/m^2
Dose of carboplatin | 300 mg/m^2 | 300 mg/m^2
Dose of cyclophosphamide | 600 mg/m^2 | 600 mg/m^2
Residual tumor < 2 cm (number of patients) | 39% (174/447) | 14% (49/342)

Clinical Response in Measurable Disease Patients

 | NCIC | SWOG
Carboplatin (number of patients) | 60% (48/80) | 58% (48/83)
Cisplatin (number of patients) | 58% (49/85) | 43% (33/76)
95% CI of difference (Carboplatin-Cisplatin) | (-13.9%, 18.6%) | (-2.3%, 31.1%)

Pathologic Complete Response*

 | NCIC | SWOG
Carboplatin (number of patients) | 11% (24/224) | 10% (17/171)
Cisplatin (number of patients) | 15% (33/223) | 10% (17/171)
95% CI of difference (Carboplatin-Cisplatin) | (-10.7%, 2.5%) | (-6.9%, 6.9%)

*114 Carboplatin and 109 Cisplatin patients did not undergo second look surgery in NCIC study.
90 Carboplatin and 106 Cisplatin patients did not undergo second look surgery in SWOG study.
Progression-Free Survival (PFS)

 | NCIC | SWOG
Median
Carboplatin | 59 weeks | 49 weeks
Cisplatin | 61 weeks | 47 weeks
2-year PFS*
Carboplatin | 31% | 21%
Cisplatin | 31% | 21%
95% CI of difference (Carboplatin-Cisplatin) | (-9.3, 8.7) | (-9, 9.4)
3-year PFS*
Carboplatin | 19% | 8%
Cisplatin | 23% | 14%
95% CI of difference (Carboplatin-Cisplatin) | (-11.5, 4.5) | (-14.1, 0.3)
Hazard Ratio** | 1.10 | 1.02
95% CI (Carboplatin-Cisplatin) | (0.89, 1.35) | (0.81, 1.29)

*Kaplan-Meier Estimates
Unrelated deaths occurring in the absence of progression were counted as events (progression) in this analysis.
**Analysis adjusted for factors found to be of prognostic significance were consistent with unadjusted analysis.
Survival

 | NCIC | SWOG
Median
Carboplatin | 110 weeks | 86 weeks
Cisplatin | 99 weeks | 79 weeks
2-year Survival*
Carboplatin | 51.9 % | 40.2 %
Cisplatin | 48.4 % | 39 %
95% CI of difference (Carboplatin-Cisplatin) | (-6.2, 13.2) | (-9.8, 12.2)
3-year Survival*
Carboplatin | 34.6 % | 18.3 %
Cisplatin | 33.1 % | 24.9 %
95% CI of difference (Carboplatin-Cisplatin) | (-7.7, 10.7) | (-15.9, 2.7)
Hazard Ratio**
95% CI (Carboplatin-Cisplatin) | 0.98 (0.78, 1.23) | 1.01 (0.78, 1.30)

*Kaplan-Meier Estimates

**Analysis adjusted for factors found to be of prognostic significance were consistent with unadjusted analysis.
Comparative Toxicity
The pattern of toxicity exerted by the carboplatin-containing regimen was significantly different from that of the cisplatin-containing combinations. Differences between the two studies may be explained by different cisplatin dosages and by different supportive care.
The carboplatin-containing regimen induced significantly more thrombocytopenia and, in one study, significantly more leukopenia and more need for transfusional support. The cisplatin-containing regimen produced significantly more anemia in one study. However, no significant differences occurred in incidences of infections and hemorrhagic episodes.
Non-hematologic toxicities (emesis, neurotoxicity, ototoxicity, renal toxicity, hypomagnesemia, and alopecia) were significantly more frequent in the cisplatin-containing arms.
ADVERSE EXPERIENCES IN PATIENTS WITH OVARIAN CANCER NCIC STUDY

 | Carboplatin Arm Percent* | Cisplatin Arm Percent* | P-Values**
Bone Marrow
Thrombocytopenia <100,000/mm^3 <50,000/mm ^3 | 70 41 | 29 6 | < 0.001 < 0.001
Neutropenia <2,000 cells/mm^3 <1000 cells/mm^3 | 97 81 | 96 79 | ns ns
Leucopenia <4,000 cells/mm^3 <2,000 cells/mm^3 | 98 68 | 97 52 | ns 0.001
Anemia <11 g/dL < 8 g/dL | 91 18 | 91 12 | ns ns
Infections | 14 | 12 | ns
Bleeding | 10 | 4 | ns
Transfusions | 42 | 31 | 0.018
Gastrointestinal
Nausea and vomiting | 93 | 98 | 0.010
Vomiting | 84 | 97 | < 0.001
Other GI side effects | 50 | 62 | 0.013
Neurologic
Peripheral neuropathies | 16 | 42 | < 0.001
Ototoxicity | 13 | 33 | < 0.001
Other sensory side effects | 6 | 10 | ns
Central neurotoxicity | 28 | 40 | 0.009
Renal
Serum creatinine elevations | 5 | 13 | 0.006
Blood urea elevations | 17 | 31 | < 0.001
Hepatic
Bilirubin elevations | 5 | 3 | ns
SGOT elevations | 17 | 13 | ns
Alkaline phosphatase elevations | - | - | -
Electrolytes loss
Sodium | 10 | 20 | 0.005
Potassium | 16 | 22 | ns
calcium | 16 | 19 | ns
Magnesium | 63 | 88 | < 0.001
Other side effects
Pain | 36 | 37 | ns
Asthenia | 40 | 33 | ns
Cardiovascular | 15 | 19 | ns
Respiratory | 8 | 9 | ns
Allergic | 12 | 9 | ns
Genitourinary | 10 | 10 | ns
Alopecia † | 50 | 62 | 0.017
Mucositis | 10 | 9 | ns

* Values are in percent of evaluable patients

** ns = not significant, p > 0.05

† May have been affected by cyclophosphamide dosage delivered
ADVERSE EXPERIENCES IN PATIENTS WITH OVARIAN CANCER SWOG STUDY

 | Carboplatin Arm Percent* | Cisplatin Arm Percent* | P-Values**
Bone Marrow
Thrombocytopenia <100,000/mm^3 <50,000/mm^3 | 59 22 | 35 11 | < 0.001 0.006
Neutropenia <2,000 cells/mm^3 <1,000 cells/mm^3 | 95 84 | 97 78 | ns ns
Leucopenia <4,000 cells/mm^3 <2,000 cells/mm^3 | 97 76 | 97 67 | ns ns
Anemia <11 g/dL < 8 g/dL | 88 8 | 87 24 | ns < 0.001
Infections | 18 | 21 | ns
Bleeding | 6 | 4 | ns
Transfusions | 25 | 33 | ns
Gastrointestinal
Nausea and vomiting | 94 | 96 | ns
Vomiting | 82 | 91 | 0.007
Other GI side effects | 40 | 48 | ns
Neurologic
Peripheral neuropathies | 13 | 28 | 0.001
Ototoxicity | 12 | 30 | < 0.001
Other sensory side effects | 4 | 6 | ns
Central neurotoxicity | 23 | 29 | ns
Renal
Serum creatinine elevations | 7 | 38 | < 0.001
Blood urea elevations | - | - | -
Hepatic
Bilirubin elevations | 5 | 3 | ns
SGOT elevations | 23 | 16 | ns
Alkaline phosphatase elevations | 29 | 20 | ns
Electrolytes loss
Sodium | - | - | -
Potassium | - | - | -
calcium | - | - | -
Magnesium | 58 | 77 | < 0.001
Other side effects
Pain | 54 | 52 | ns
Asthenia | 43 | 46 | ns
Cardiovascular | 23 | 30 | ns
Respiratory | 12 | 11 | ns
Allergic | 10 | 11 | ns
Genitourinary | 11 | 13 | ns
Alopecia † | 43 | 57 | 0.009
Mucositis | 6 | 11 | ns

* Values are in percent of evaluable patients

** ns = not significant, p > 0.05

† May have been affected by cyclophosphamide dosage delivered
Use as a Single Agent for Secondary Treatment of Advanced Ovarian Cancer
In two prospective, randomized controlled studies in patients with advanced ovarian cancer previously treated with chemotherapy, carboplatin achieved 6 clinical complete responses in 47 patients. The duration of these responses ranged from 45 to 71+ weeks.

INDICATIONS

Initial Treatment of Advanced Ovarian Carcinoma
Carboplatin injection is indicated for the initial treatment of advanced ovarian carcinoma in established combination with other approved chemotherapeutic agents. One established combination regimen consists of carboplatin and cyclophosphamide. Two randomized controlled studies conducted by the NCIC and SWOG with carboplatin versus cisplatin, both in combination with cyclophosphamide, have demonstrated equivalent overall survival between the two groups (see CLINICAL STUDIES).
There is limited statistical power to demonstrate equivalence in overall pathologic complete response rates and long-term survival (≥ 3 years) because of the small number of patients with these outcomes: the small number of patients with residual tumor < 2 cm after initial surgery also limits the statistical power to demonstrate equivalence in this subgroup.
Secondary Treatment of Advanced Ovarian Carcinoma
Carboplatin injection is indicated for the palliative treatment of patients with ovarian carcinoma recurrent after prior chemotherapy, including patients who have been previously treated with cisplatin.
Within the group of patients previously treated with cisplatin, those who have developed progressive disease while receiving cisplatin therapy may have a decreased response rate.

CONTRAINDICATIONS

Carboplatin injection is contraindicated in patients with a history of severe allergic reactions to cisplatin or other platinum-containing compounds.
Carboplatin injection should not be employed in patients with severe bone marrow depression or significant bleeding.

WARNINGS

Bone marrow suppression (leukopenia, neutropenia, and thrombocytopenia) is dose-dependent and is also the dose-limiting toxicity. Peripheral blood counts should be frequently monitored during carboplatin injection treatment and, when appropriate, until recovery is achieved. Median nadir occurs at day 21 in patients receiving single agent carboplatin. In general, single intermittent courses of carboplatin should not be repeated until leukocyte, neutrophil, and platelet counts have recovered.
Since anemia is cumulative, transfusions may be needed during treatment with carboplatin, particularly in patients receiving prolonged therapy.
Bone marrow suppression is increased in patients who have received prior therapy, especially regimens including cisplatin. Marrow suppression is also increased in patients with impaired kidney function. Initial carboplatin injection dosages in these patients should be appropriately reduced (see DOSAGE AND ADMINISTRATION) and blood counts should be carefully monitored between courses. The use of carboplatin in combination with other bone marrow suppressing therapies must be carefully managed with respect to dosage and timing in order to minimize additive effects.
Carboplatin has limited nephrotoxic potential, but concomitant treatment with aminoglycosides has resulted in increased renal and/or audiologic toxicity, and caution must be exercised when a patient receives both drugs. Clinically significant hearing loss has been reported to occur in pediatric patients when carboplatin was administered at higher than recommended doses in combination with other ototoxic agents.
Carboplatin can induce emesis, which can be more severe in patients previously receiving emetogenic therapy. The incidence and intensity of emesis have been reduced by using premedication with antiemetics. Although no conclusive efficacy data exist with the following schedules of carboplatin, lengthening the duration of single intravenous administration to 24 hours or dividing the total dose over five consecutive daily pulse doses has resulted in reduced emesis.
Although peripheral neurotoxicity is infrequent, its incidence is increased in patients older than 65 years and in patients previously treated with cisplatin. Pre-existing cisplatin-induced neurotoxicity does not worsen in about 70% of the patients receiving carboplatin as secondary treatment.
Loss of vision, which can be complete for light and colors, has been reported after the use of carboplatin with doses higher than those recommended in the package insert. Vision appears to recover totally or to a significant extent within weeks of stopping these high doses.
As in the case of other platinum-coordination compounds, allergic reactions to carboplatin have been reported. These may occur within minutes of administration and should be managed with appropriate supportive therapy. There is increased risk of allergic reactions including anaphylaxis in patients previously exposed to platinum therapy (see CONTRAINDICATIONSand ADVERSE REACTIONS, Allergic Reactions).
High dosages of carboplatin (more than 4 times the recommended dose) have resulted in severe abnormalities of liver function tests.
Carboplatin injection may cause fetal harm when administered to a pregnant woman. Carboplatin has been shown to be embryotoxic and teratogenic in rats. There are no adequate and well-controlled studies in pregnant women. If this drug is used during pregnancy, or if the patient becomes pregnant while receiving this drug, the patient should be apprised of the potential hazard to the fetus. Women of childbearing potential should be advised to avoid becoming pregnant.

PRECAUTIONS

General

Needles or intravenous administration sets containing aluminum parts that may come in contact with carboplatin injection should not be used for the preparation or administration of the drug. Aluminum can react with carboplatin causing precipitate formation and loss of potency.

Drug Interactions

The renal effects of nephrotoxic compounds may be potentiated by carboplatin.

Carcinogenesis & Mutagenesis & Impairment Of Fertility

The carcinogenic potential of carboplatin has not been studied, but compounds with similar mechanisms of action and mutagenicity profiles have been reported to be carcinogenic. Carboplatin has been shown to be mutagenic both in vitroand in vivo. It has also been shown to be embryotoxic and teratogenic in rats receiving the drug during organogenesis. Secondary malignancies have been reported in association with multi-drug therapy.

Pregnancy

Pregnancy Category D (See WARNINGS).

Nursing Mothers

It is not known whether carboplatin is excreted in human milk. Because there is a possibility of toxicity in nursing infants secondary to carboplatin treatment of the mother, it is recommended that breast feeding be discontinued if the mother is treated with carboplatin injection.

Pediatric Use

Safety and effectiveness in pediatric patients have not been established (see WARNINGS, "audiologic toxicity").

Geriatric Use

Of the 789 patients in initial treatment combination therapy studies (NCIC and SWOG), 395 patients were treated with carboplatin in combination with cyclophosphamide. Of these, 141 were over 65 years of age and 22 were 75 years or older. In these trials, age was not a prognostic factor for survival. In terms of safety, elderly patients treated with carboplatin were more likely to develop severe thrombocytopenia than younger patients. In a combined database of 1,942 patients (414 were ≥ 65 years of age) that received single agent carboplatin for different tumor types, a similar incidence of adverse events was seen in patients 65 years and older and in patients less than 65. Other reported clinical experience has not identified differences in responses between elderly and younger patients, but greater sensitivity of some older individuals cannot be ruled out. Because renal function is often decreased in the elderly, renal function should be considered in the selection of carboplatin injection dosage (see DOSAGE AND ADMINISTRATION).

ADVERSE REACTIONS

To report SUSPECTED ADVERSE REACTIONS, contact BPI Labs, LLC at (727) 471-0850 or FDA at 1-800-FDA-1088 or www.fda.gov/medwatch.

For a comparison of toxicities when carboplatin or cisplatin was given in combination with cyclophosphamide, see CLINICAL STUDIES, Use with Cyclophosphamide for Initial Treatment of Ovarian Cancer, Comparative Toxicity.
ADVERSE EXPERIENCES IN PATIENTS WITH OVARIAN CANCER

 | First Line Combination Therapy* Percent | Second Line Single Agent Therapy** Percent
Bone Marrow
Thrombocytopenia <100,000/mm^3 <50,000/mm^3 | 66 33 | 62 35
Neutropenia <2,000 cells/mm^3 <1,000 cells/mm^3 | 96 82 | 67 21
Leucopenia <4,000 cells/mm^3 <2,000 cells/mm^3 | 97 71 | 85 26
Anemia <11 g/dL < 8 g/dL | 90 14 | 90 21
Infections | 16 | 5
Bleeding | 8 | 5
Transfusions | 35 | 44
Gastrointestinal
Nausea and vomiting | 93 | 92
Vomiting | 83 | 81
Other GI side effects | 46 | 21
Neurologic
Peripheral neuropathies | 15 | 6
Ototoxicity | 12 | 1
Other sensory side effects | 5 | 1
Central neurotoxicity | 26 | 5
Renal
Serum creatinine elevations | 6 | 10
Blood urea elevations | 17 | 22
Hepatic
Bilirubin elevations | 5 | 5
SGOT elevations | 20 | 19
Alkaline phosphatase elevations | 29 | 37
Electrolytes loss
Sodium | 10 | 47
Potassium | 16 | 28
calcium | 16 | 31
Magnesium | 61 | 43
Other side effects
Pain | 44 | 23
Asthenia | 41 | 11
Cardiovascular | 19 | 6
Respiratory | 10 | 6
Allergic | 11 | 2
Genitourinary | 10 | 2
Alopecia | 49 | 2
Mucositis | 8 | 1

* Use with Cyclophosphamide for Initial Treatment of Ovarian Cancer:Data are based on the experience of 393 patients with ovarian cancer (regardless of baseline status) who received initial combination therapy with carboplatin and cyclophosphamide in two randomized controlled studies conducted by SWOG and NCIC (see CLINICAL STUDIES).
Combination with cyclophosphamide as well as duration of treatment may be responsible for the differences that can be noted in the adverse experience table.
** Single Agent Use for the Secondary Treatment of Ovarian Cancer:Data are based on the experience of 553 patients with previously treated ovarian carcinoma (regardless of baseline status) who received single agent carboplatin.
In the narrative section that follows, the incidences of adverse events are based on data from 1,893 patients with various types of tumors who received carboplatin as single agent therapy.
Hematologic Toxicity
Bone marrow suppression is the dose-limiting toxicity of carboplatin. Thrombocytopenia with platelet counts below 50,000/mm ^3occurs in 25% of the patients (35% of pretreated ovarian cancer patients); neutropenia with granulocyte counts below 1,000/mm ^3occurs in 16% of the patients (21% of pretreated ovarian cancer patients); leukopenia with WBC counts below 2,000/mm ^3occurs in 15% of the patients (26% of pretreated ovarian cancer patients). The nadir usually occurs about day 21 in patients receiving single agent therapy. By day 28, 90% of patients have platelet counts above 100,000/mm ^3; 74% have neutrophil counts above 2,000/mm ^3; 67% have leukocyte counts above 4,000/mm ^3.
Marrow suppression is usually more severe in patients with impaired kidney function. Patients with poor performance status have also experienced a higher incidence of severe leukopenia and thrombocytopenia.
The hematologic effects, although usually reversible, have resulted in infectious or hemorrhagic complications in 5% of the patients treated with carboplatin, with drug related death occurring in less than 1% of the patients. Fever has also been reported in patients with neutropenia.
Anemia with hemoglobin less than 11 g/dL has been observed in 71% of the patients who started therapy with a baseline above that value. The incidence of anemia increases with increasing exposure to carboplatin. Transfusions have been administered to 26% of the patients treated with carboplatin (44% of previously treated ovarian cancer patients).
Bone marrow depression may be more severe when carboplatin is combined with other bone marrow suppressing drugs or with radiotherapy.
Gastrointestinal Toxicity
Vomiting occurs in 65% of the patients (81% of previously treated ovarian cancer patients) and in about one-third of these patients it is severe. Carboplatin, as a single agent or in combination, is significantly less emetogenic than cisplatin; however, patients previously treated with emetogenic agents, especially cisplatin, appear to be more prone to vomiting. Nausea alone occurs in an additional 10% to 15% of patients. Both nausea and vomiting usually cease within 24 hours of treatment and are often responsive to antiemetic measures. Although no conclusive efficacy data exist with the following schedules, prolonged administration of carboplatin, either by continuous 24-hour infusion or by daily pulse doses given for 5 consecutive days, was associated with less severe vomiting than the single-dose intermittent schedule. Emesis was increased when carboplatin was used in combination with other emetogenic compounds. Other gastrointestinal effects observed frequently were pain, in 17% of the patients; diarrhea, in 6%; and constipation, also in 6%.
Neurologic Toxicity
Peripheral neuropathies have been observed in 4% of the patients receiving carboplatin (6% of pretreated ovarian cancer patients) with mild paresthesias occurring most frequently. Carboplatin therapy produces significantly fewer and less severe neurologic side effects than does therapy with cisplatin. However, patients older than 65 years and/or previously treated with cisplatin appear to have an increased risk (10%) for peripheral neuropathies. In 70% of the patients with pre-existing cisplatin induced peripheral neurotoxicity, there was no worsening of symptoms during therapy with carboplatin. Clinical ototoxicity and other sensory abnormalities such as visual disturbances and change in taste have been reported in only 1% of the patients. Central nervous system symptoms have been reported in 5% of the patients and appear to be most often related to the use of antiemetics.
Although the overall incidence of peripheral neurologic side effects induced by carboplatin is low, prolonged treatment, particularly in cisplatin pretreated patients, may result in cumulative neurotoxicity.
Nephrotoxicity
Development of abnormal renal function test results is uncommon, despite the fact that carboplatin, unlike cisplatin, has usually been administered without high-volume fluid hydration and/or forced diuresis. The incidences of abnormal renal function tests reported are 6% for serum creatinine and 14% for blood urea nitrogen (10% and 22%, respectively, in pretreated ovarian cancer patients). Most of these reported abnormalities have been mild and about one-half of them were reversible.
Creatinine clearance has proven to be the most sensitive measure of kidney function in patients receiving carboplatin, and it appears to be the most useful test for correlating drug clearance and bone marrow suppression. Twenty-seven percent of the patients who had a baseline value of 60 mL/min or more demonstrated a reduction below this value during carboplatin therapy.

Hepatic Toxicity
The incidences of abnormal liver function tests in patients with normal baseline values were reported as follows: total bilirubin, 5%; SGOT, 15%; and alkaline phosphatase, 24%; (5%, 19%, and 37%, respectively, in pretreated ovarian cancer patients). These abnormalities have generally been mild and reversible in about one-half of the cases, although the role of metastatic tumor in the liver may complicate the assessment in many patients. In a limited series of patients receiving very high dosages of carboplatin and autologous bone marrow transplantation, severe abnormalities of liver function tests were reported.
Electrolyte Changes
The incidences of abnormally decreased serum electrolyte values reported were as follows: sodium, 29%; potassium, 20%; calcium, 22%; and magnesium, 29%; (47%, 28%, 31%, and 43%, respectively, in pretreated ovarian cancer patients). Electrolyte supplementation was not routinely administered concomitantly with carboplatin, and these electrolyte abnormalities were rarely associated with symptoms.
Allergic Reactions
Hypersensitivity to carboplatin has been reported in 2% of the patients. These allergic reactions have been similar in nature and severity to those reported with other platinum-containing compounds, i.e. rash, urticaria, erythema, pruritus, and rarely bronchospasm and hypotension. Anaphylactic reactions have been reported as part of postmarketing surveillance (see WARNINGS). These reactions have been successfully managed with standard epinephrine, corticosteroid, and antihistamine therapy.
Injection Site Reactions
Injection site reactions, including redness, swelling, and pain, have been reported during postmarketing surveillance. Necrosis associated with extravasation has also been reported.
Other Events
Pain and asthenia were the most frequently reported miscellaneous adverse effects; their relationship to the tumor and to anemia was likely. Alopecia was reported (3%). Cardiovascular, respiratory, genitourinary, and mucosal side effects have occurred in 6% or less of the patients. Cardiovascular events (cardiac failure, embolism, cerebrovascular accidents) were fatal in less than 1% of the patients and did not appear to be related to chemotherapy. Cancer-associated hemolytic uremic syndrome has been reported rarely.
Malaise, anorexia, hypertension, dehydration, and stomatitis have been reported as part of postmarketing surveillance.

OVERDOSAGE

There is no known antidote for carboplatin injection overdosage. The anticipated complications of overdosage would be secondary to bone marrow suppression and/or hepatic toxicity.

DOSAGE & ADMINISTRATION

NOTE: Aluminum reacts with carboplatin causing precipitate formation and loss of potency, therefore, needles or intravenous sets containing aluminum parts that may come in contact with the drug must not be used for the preparation or administration of carboplatin injection.
Single Agent Therapy
Carboplatin injection, as a single agent, has been shown to be effective in patients with recurrent ovarian carcinoma at a dosage of 360 mg/m^2IV on day 1 every 4 weeks (alternatively see Formula Dosing). In general, however, single intermittent courses of carboplatin should not be repeated until the neutrophil count is at least 2,000 and the platelet count is at least 100,000.
Combination Therapy with Cyclophosphamide

In the chemotherapy of advanced ovarian cancer, an effective combination for previously untreated patients consists of:

Carboplatin - 300 mg/m^2IV on day 1 every 4 weeks for 6 cycles (alternatively see Formula Dosing).

Cyclophosphamide - 600 mg/m^2IV on day 1 every 4 weeks for 6 cycles. For directions regarding the use and administration of cyclophosphamide please refer to its package insert (see CLINICAL STUDIES).
Intermittent courses of carboplatin in combination with cyclophosphamide should not be repeated until the neutrophil count is at least 2,000 and the platelet count is at least 100,000.
Dose Adjustment Recommendations
Pretreatment platelet count and performance status are important prognostic factors for severity of myelosuppression in previously treated patients.
The suggested dose adjustments for single agent or combination therapy shown in the table below are modified from controlled trials in previously treated and untreated patients with ovarian carcinoma. Blood counts were done weekly, and the recommendations are based on the lowest post-treatment platelet or neutrophil value.

Platelets | Neutrophils | Adjusted Dose* (From Prior Course)
> 100,000 | > 2,000 | 125%
50 to 100,000 | 500 to 2,000 | No adjustment
< 50,000 | < 500 | 75%

* Percentages apply to carboplatin injection as a single agent or to both carboplatin and cyclophosphamide combination. In the controlled studies, dosages were also adjusted at a lower level (50% to 60%) for severe myelosuppression. Escalations above 125% were not recommended for these studies.
Carboplatin injection is usually administered by an infusion lasting 15 minutes or longer. No pre- or post-treatment hydration or forced diuresis is required.
Patients with Impaired Kidney Function
Patients with creatinine clearance values below 60 mL/min are at increased risk of severe bone marrow suppression. In renally-impaired patients who received single agent carboplatin therapy, the incidence of severe leukopenia, neutropenia, or thrombocytopenia has been about 25% when the dosage modifications in the table below have been used.

Baseline Creatinine Clearance | Recommended Dose on Day 1
41 to 59 mL/min | 250 mg/m^2
16 to 40 mL/min | 200 mg/m^2

The data available for patients with severely impaired kidney function (creatinine clearance below 15 mL/min) are too limited to permit a recommendation for treatment.
These dosing recommendations apply to the initial course of treatment. Subsequent dosages should be adjusted according to the patient's tolerance based on the degree of bone marrow suppression.
Formula Dosing
Another approach for determining the initial dose of carboplatin injection is the use of mathematical formulae, which are based on a patient's pre-existing renal function or renal function and desired platelet nadir. Renal excretion is the major route of elimination for carboplatin (see CLINICAL PHARMACOLOGY). The use of dosing formulae, as compared to empirical dose calculation based on body surface area, allows compensation for patient variations in pretreatment renal function that might otherwise result in either underdosing (in patients with above average renal function) or overdosing (in patients with impaired renal function).

A simple formula for calculating dosage, based upon a patient's glomerular filtration rate (GFR in mL/min) and carboplatin injection target area under the concentration versus time curve (AUC in mg/mL ·min), has been proposed by Calvert. In these studies, GFR was measured by^51Cr-EDTA clearance.

CALVERT FORMULA FOR CARBOPLATIN DOSING

Total Dose (mg) = (target AUC) × (GFR + 25)
Note: With the Calvert formula, the total dose of carboplatin is calculated in mg, notmg/m^2.

The target AUC of 4 mg/mL ·min to 6 mg/mL ·min using single agent carboplatin appears to provide the most appropriate dose range in previously treated patients. This study also showed a trend between the AUC of single agent carboplatin administered to previously treated patients and the likelihood of developing toxicity.

 | % Actual Toxicity in Previously Treated Patients
AUC (mg/mL ·min) | Gr 3 or Gr 4 Thrombocytopenia | Gr 3 or Gr 4 Leukopenia
4 to 5 | 16% | 13%
6 to 7 | 33% | 34%

Geriatric Dosing
Because renal function is often decreased in elderly patients, formula dosing of carboplatin injection based on estimates of GFR should be used in elderly patients to provide predictable plasma carboplatin injection AUCs and thereby minimize the risk of toxicity.
PREPARATION OF INTRAVENOUS SOLUTIONS
Carboplatin injection is a premixed aqueous solution of 10 mg/mL carboplatin.
Carboplatin aqueous solution can be further diluted to concentrations as low as 0.5 mg/mL with 5% Dextrose in Water (D5W) or 0.9% Sodium Chloride Injection, USP.
When prepared as directed, carboplatin aqueous solutions are stable for 8 hours at room temperature (25°C). Since no antibacterial preservative is contained in the formulation, it is recommended that carboplatin aqueous solutions be discarded 8 hours after dilution.

HOW SUPPLIED

Carboplatin injection,USP is available in multi-dose vials, individually cartoned:

NDC Number | Fill volume | Package
54288-164-01 | 5 mL fill in 10 mL Multiple dose vial | One Multiple dose vial in one carton
54288-165-01 | 15 mL fill in 20 mL Multiple dose vial | One Multiple dose vial in one carton
54288-166-01 | 45 mL fill in 50 mL Multiple dose vial | One Multiple dose vial in one carton
54288-167-01 | 60 mL fill in 100 mL Multiple dose vial | One Multiple dose vial in one carton

STORAGE
Unopened vials of carboplatin injection are stable to the date indicated on the package when stored at 20° to 25°C (68° to 77°F) [See USP Controlled Room Temperature].
PROTECT FROM LIGHT.

Carboplatin injection multi dose vials maintain microbial, chemical, and physical stability for up to 14 days at 25°C following multiple needle entries.
Parenteral drug products should be inspected visually for particulate matter and discoloration prior to administration. Solutions for infusion should be discarded 8 hours after preparation.
HANDLING AND DISPOSAL
Caution should be exercised in handling and preparing carboplatin injection. Several guidelines on this subject have been published ^1-4.
To minimize the risk of dermal exposure, always wear impervious gloves when handling vials containing carboplatin injection. If carboplatin injection contacts the skin, immediately wash the skin thoroughly with soap and water. If carboplatin contacts mucous membranes, the membranes should be flushed immediately and thoroughly with water. More information is available in the references listed below.

REFERENCES

1.NIOSH Alert: Preventing occupational exposures to antineoplastic and other hazardous drugs in healthcare settings. 2004. U.S. Department of Health and Human Services, Public Health Service, Centers for Disease Control and Prevention, National Institute for Occupational Safety and Health, DHHS (NIOSH) Publication No. 2004-165.
2.OSHA Technical Manual, TED 1-0.15A, Section VI: Chapter 2. Controlling occupational exposure to hazardous drugs. OSHA, 1999. http://www.osha.gov/dts/osta/otm/otm_vi/otm_vi_2.html
3.American Society of Health-System Pharmacists. ASHP guidelines on handling hazardous drugs. Am J Health-Syst Pharm. 2006; 63:1172-1193.
4.Polovich M, White JM, Kelleher LO, eds. 2005. Chemotherapy and biotherapy guidelines and recommendations for practice. 2nd ed. Pittsburgh, PA: Oncology Nursing Society.

Manufactured for:
BPI Labs, LLC
12393 Belcher Rd S, Suite 450
Largo, FL 33773 USA

Made in India

November 2023

Patient Insert
Carboplatin Injection, USP
Rx only
Read this entire leaflet carefully. Keep it for future reference.
This information will help you learn more about carboplatin. It cannot, however, cover all the possible warnings or side effects relating to carboplatin, and it does not list all of the benefits and risks of carboplatin. Your doctor should always be your first choice for detailed information about your medical condition and your treatment. Be sure to ask your doctor about any questions you may have.
What is cancer?
Under normal conditions, the cells in your body divide and grow in an orderly, controlled fashion. Cell division and growth are necessary for the human body to perform its functions and to repair itself. Cancer cells are different from normal cells because they are not able to control their own growth. The reasons for this abnormal growth are not yet fully understood.
A tumor is a mass of unhealthy cells that are dividing and growing fast and in an uncontrolled way. When a tumor invades surrounding healthy body tissue it is known as a malignant tumor. A malignant tumor can spread (metastasize) from its original location to other parts of the body.
What is carboplatin?
Carboplatin is a medicine that is used to treat cancer of the ovaries. It acts by interfering with the division of rapidly multiplying cells, particularly cancer cells.
Who should not take carboplatin?
Treatment with carboplatin is not recommended if you:
• are allergic to carboplatin or other platinum-containing products;
• have a weakened blood-forming system (bone marrow depression) or significant bleeding;
• are pregnant, intend to become pregnant, or are breastfeeding a baby.
How is carboplatin used?
Only a professional experienced in the use of cancer drugs should give you this medication. Carboplatin is given by dripping the medicine slowly and directly into a vein (intravenous infusion) for 15 minutes or longer. Your doctor will determine the dose of carboplatin for you based on your weight, height, and kidney function. Carboplatin may be given alone or with other drugs. Treatment is usually repeated every four weeks for a number of cycles.
Before and after carboplatin treatment, your doctor may give you medication to lessen the nausea and vomiting associated with this cancer treatment
What should you tell your doctor before starting treatment with carboplatin?
Discuss the benefits and risks of carboplatin with your doctor before beginning treatment.
Be sure to inform your doctor:
• If you are allergic to carboplatin or other platinum-containing products;
• If you are or intend to become pregnant, since carboplatin may harm the developing fetus. It is important to use effective birth control while you are being treated with carboplatin.
• If you are breastfeeding, since nursing infants may be exposed to carboplatin in this way;
• If you are taking other medicines, including all prescription and non-prescription (over-the-counter) drugs, since carboplatin may affect the action of other medicines;
• If you have any other medical problems, especially chicken pox (including recent exposure to adults or children with chicken pox), shingles, hearing problems, infection, or kidney disease, since treatment with carboplatin increases the risk and severity of these conditions.
What should I avoid while taking carboplatin?
If you are pregnant or think you might be pregnant, or if you are breastfeeding, let your doctor know right away. Carboplatin may harm your developing fetus or breastfeeding baby. If you are a woman of child bearing age, you should use birth control to avoid getting pregnant while you are taking carboplatin.
You should avoid contact with adults and children who have infections, and tell your doctor right away if you show signs of infection such as cough, fever, and/or chills. Also, while you are being treated with carboplatin or after you stop treatment, first check with your doctor beforegetting any immunizations (vaccinations). Avoid contact with adults or children who have received oral polio vaccine since they can pass the polio virus to you.
What are the possible side effects of carboplatin?
Carboplatin may cause unwanted effects, particularly because carboplatin interferes with the growth of normal cells as well as cancer cells. For example, the occurrence of another cancer (secondary malignancy) has been reported in patients receiving cancer chemotherapy with multiple drugs. It is not always possible to tell whether such effects are caused by carboplatin, another drug you may be taking, or your illness. Because some of these effects may be serious, you will need close medical supervision during treatment with carboplatin.
The most serious side effects of carboplatin are:
• bleeding and reduced blood cells , including reduced red blood cells (anemia) and platelets (needed for proper blood clotting), which may be severe enough to require blood transfusion. You should tell your doctor right away if you notice any unusual bruising or bleeding, including black tarry stools or blood in the urine.
• infection– carboplatin can temporarily lower the number of white blood cells in your blood, increasing the risk of infection;
• life-threatening allergic reaction– during and after treatment the doctor or nurse will observe you carefully for signs of allergic reaction;
• kidney and liver problems ;
• loss of hearing or ringing in the ears ;
Contact your doctor right away if you experience any of these effects, or notice effects that worry you or are troublesome.
Of the less serious side effectsassociated with carboplatin treatment, the most common are nausea, vomiting, diarrhea, loss of appetite, hair loss and numbness, tingling, burning, or pain in the hands and feet.
This medicine was prescribed for your particular condition. It must be given under close medical supervision by a doctor trained in the use of drugs for the treatment of cancer.
This summary does not include everything there is to know about carboplatin. Medicines are sometimes prescribed for purposes other than those listed in patient leaflets. If you have questions or concerns, or want more information about carboplatin, your physician and pharmacist have the complete prescribing information upon which this information is based. You may want to read it and discuss it with your doctor. Remember, no written summary can replace careful discussion with your doctor.

Manufactured for:
BPI Labs, LLC
12393 Belcher Rd S, Suite 450
Largo, FL 33773 USA

Made in India

November 2023

LI54I-55I-56I-57I R-2311

PACKAGE LABEL.PRINCIPAL DISPLAY PANEL

Carboplatin Injection, USP 50 mg/5 mL Vial Label Text

NDC 54288-164-01 Rx only

Carboplatin Injection, USP

50 mg/5 mL

(10 mg/mL)

For Intravenous Use Only

Sterile, Aqueous solution

Cytotoxic Agent

5 mL Multi-Dose Vial

Carboplatin Injection, USP 50 mg/5 mL Vial Carton Text

NDC 54288-164-01 Rx only

Carboplatin Injection, USP

50 mg/5 mL

(10 mg/mL)

For Intravenous Use Only
Sterile, Aqueous solution

Cytotoxic Agent

5 mL Multi-Dose Vial

Carboplatin Injection, USP 150 mg/15 mL Vial Label Text

NDC 54288-165-01 Rx only

Carboplatin Injection, USP

150 mg/15 mL

(10 mg/mL)
For Intravenous Use Only
Sterile, Aqueous solution

Cytotoxic Agent

15 mL Multi-Dose Vial

Carboplatin Injection, USP 150 mg/15 mL Vial Carton Text

NDC 54288-165-01 Rx only

Carboplatin Injection, USP

150 mg/15 mL

(10 mg/mL)
For Intravenous Use Only
Sterile, Aqueous solution

Cytotoxic Agent

15 mL Multi-Dose Vial

Carboplatin Injection, USP 450 mg/45 mL Vial Label Text

NDC 54288-166-01 Rx only
Carboplatin Injection, USP
450 mg/45 mL
(10 mg/mL)
For Intravenous Use Only
Sterile, Aqueous solution

Cytotoxic Agent

45 mL Multi-Dose Vial

Carboplatin Injection, USP 450 mg/45 mL Vial Carton Text

NDC 54288-166-01 Rx only
Carboplatin Injection, USP
450 mg/45 mL
(10 mg/mL)
For Intravenous Use Only
Sterile, Aqueous solution

Cytotoxic Agent

45 mL Multi-Dose Vial

Carboplatin Injection, USP 600 mg/60 mL Vial Label Text

NDC 54288-167-01 Rx only
Carboplatin Injection, USP
600 mg/60 mL
(10 mg/mL)
For Intravenous Use Only
Sterile, Aqueous solution

Cytotoxic Agent

60 mL Multi-Dose Vial

Carboplatin Injection, USP 600 mg/60 mL Vial Carton Text

NDC 54288-167-01 Rx only
Carboplatin Injection, USP
600 mg/60 mL
(10 mg/mL)
For Intravenous Use Only
Sterile, Aqueous solution

Cytotoxic Agent

60 mL Multi-Dose Vial